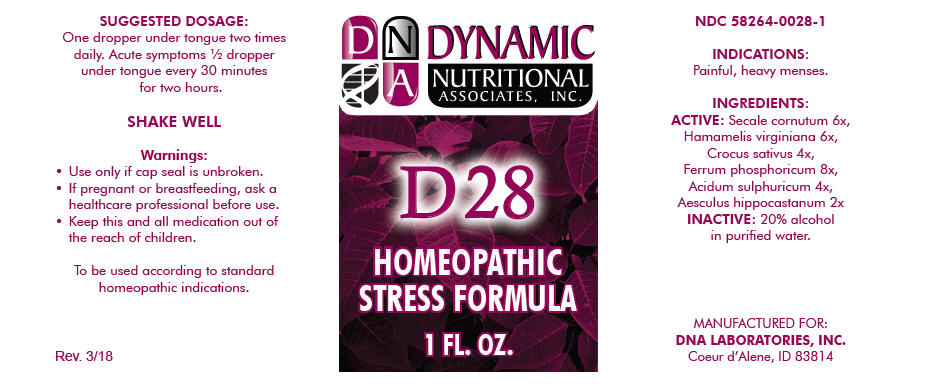 DRUG LABEL: D-28
NDC: 58264-0028 | Form: SOLUTION/ DROPS
Manufacturer: DNA Labs, Inc.
Category: homeopathic | Type: HUMAN OTC DRUG LABEL
Date: 20250113

ACTIVE INGREDIENTS: CLAVICEPS PURPUREA SCLEROTIUM 6 [hp_X]/1 mL; HAMAMELIS VIRGINIANA ROOT BARK/STEM BARK 6 [hp_X]/1 mL; SAFFRON 4 [hp_X]/1 mL; FERROSOFERRIC PHOSPHATE 8 [hp_X]/1 mL; SULFURIC ACID 4 [hp_X]/1 mL; HORSE CHESTNUT 2 [hp_X]/1 mL
INACTIVE INGREDIENTS: ALCOHOL; WATER

D-28

NDC 58264-0028-1

INDICATIONS

PURPOSE

Painful, heavy menses.

INGREDIENTS

ACTIVE

Secale cornutum 6x, Hamamelis virginiana 6x, Crocus sativus 4x, Ferrum phosphoricum 8x, Acidum sulphuricum 4x, Aesculus hippocastanum 2x

INACTIVE

20% alcohol in purified water.

SUGGESTED DOSAGE

One dropper under tongue two times daily. Acute symptoms ½ dropper under tongue every 30 minutes for two hours.

STORAGE AND HANDLING

SHAKE WELL

Warnings

- Use only if cap seal is unbroken.

PREGNANCY OR BREAST FEEDING

- If pregnant or breastfeeding, ask a healthcare professional before use.

KEEP OUT OF REACH OF CHILDREN

- Keep this and all medication out of the reach of children.

To be used according to standard homeopathic indications.

PRINCIPAL DISPLAY PANEL - 1 FL. OZ. Bottle Label

DYNAMIC
NUTRITIONAL
ASSOCIATES, INC.

D 28

HOMEOPATHIC
STRESS FORMULA

1 FL. OZ.